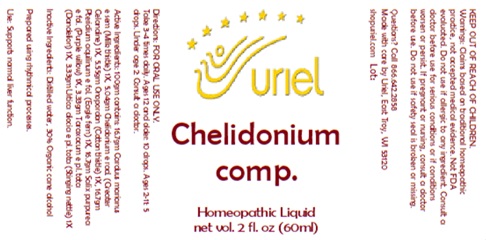 DRUG LABEL: Chelidonium comp.
NDC: 48951-3281 | Form: LIQUID
Manufacturer: Uriel Pharmacy, Inc
Category: homeopathic | Type: HUMAN OTC DRUG LABEL
Date: 20250212

ACTIVE INGREDIENTS: PTERIDIUM AQUILINUM WHOLE 1 [hp_X]/1 mL; TARAXACUM PALUSTRE ROOT 1 [hp_X]/1 mL; URTICA DIOICA 1 [hp_X]/1 mL; CHELIDONIUM MAJUS ROOT 1 [hp_X]/1 mL; MILK THISTLE 1 [hp_X]/1 mL; SALIX PURPUREA BARK 1 [hp_X]/1 mL; ONOPORDUM ACANTHIUM FLOWER 1 [hp_X]/1 mL
INACTIVE INGREDIENTS: WATER; ALCOHOL

Chelidonium comp.

INDICATIONS AND USAGE

Directions: FOR ORAL USE ONLY.

DOSAGE AND ADMINISTRATION

Take 3-4 times daily. Ages 12 and older: 10 drops. Ages 2-11: 5 drops. Under age 2: Consult a doctor.

ACTIVE INGREDIENT

Active Ingredients: 100gm contains: 16.7gm Carduus marianus e sem (Milk thistle) 1X, 5.04gm Chelidonium e rad. (Greater Celandine) 1X, 5.55gm Onopordon (Cotton thistle) 1X, 16.7gm Pteridium aquilinum e fol. (Eagle fern) 1X, 16.7gm Salix purpurea e fol. (Purple willow) 1X, 3.33gm Taraxacum e pl. tota (Dandelion) 1X, 3.33gm Urtica diocia e pl. tota (Stinging nettle) 1X

Inactive Ingredients: Distilled water, 30% Organic cane alcohol

Prepared using rhythmical processes.

PURPOSE

Use: Supports normal liver function.

KEEP OUT OF REACH OF CHILDREN.

WARNINGS

Warnings: Claims based on traditional homeopathic practice, not accepted medical evidence. Not FDA evaluated. Do not use if allergic to any ingredient. Consult a doctor before use for serious conditions or if conditions worsen or persist. If pregnant or nursing, consult a doctor before use. Do not use if safety seal is broken or missing.

Questions? Call 866.642.2858
Made with care by Uriel, East Troy, WI 53120
shopuriel.com Lot: